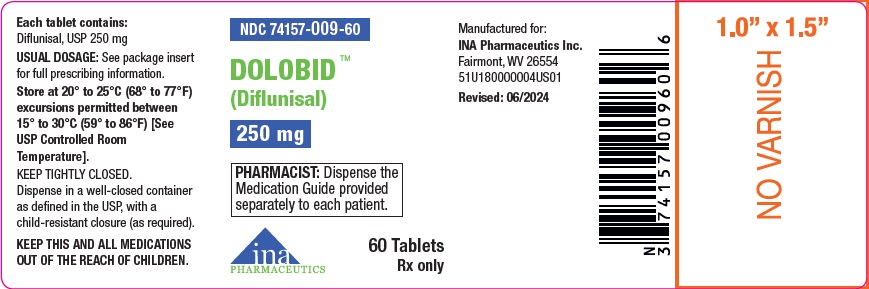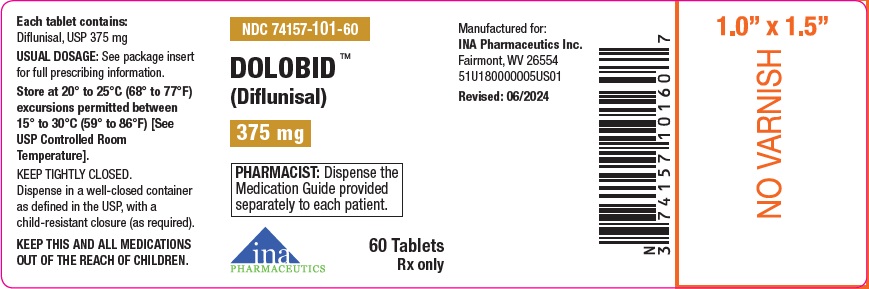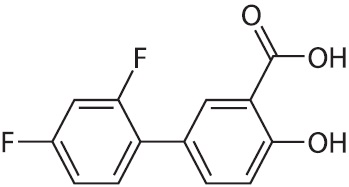 DRUG LABEL: Dolobid
NDC: 74157-009 | Form: TABLET, FILM COATED
Manufacturer: INA Pharmaceutics Inc
Category: prescription | Type: HUMAN PRESCRIPTION DRUG LABEL
Date: 20251006

ACTIVE INGREDIENTS: DIFLUNISAL 250 mg/1 1
INACTIVE INGREDIENTS: MICROCRYSTALLINE CELLULOSE; CROSCARMELLOSE SODIUM; STARCH, CORN; SODIUM STEARYL FUMARATE; HYPROMELLOSE, UNSPECIFIED; TITANIUM DIOXIDE; PROPYLENE GLYCOL; FD&C BLUE NO. 2 ALUMINUM LAKE

Dolobid™ (Diflunisal), 250 mg and 375 mg

BOXED WARNING

Cardiovascular Thrombotic Events

- Nonsteroidal anti-inflammatory drugs (NSAIDs) cause an increased risk of serious cardiovascular thrombotic events, including myocardial infarction and stroke, which can be fatal. This risk may occur early in treatment and may increase with duration of use (see WARNINGSand PRECAUTIONS).
- Dolobid is contraindicated in the setting of coronary artery bypass graft (CABG) surgery (see CONTRAINDICATIONand WARNINGS).

Gastrointestinal Risk

- NSAIDs cause an increased risk of serious gastrointestinal adverse events including bleeding, ulceration, and perforation of the stomach or intestines, which can be fatal. These events can occur at any time during use and without warning symptoms. Elderly patients are at greater risk for serious gastrointestinal events (see WARNINGS).

DESCRIPTION

Diflunisal, USP is [1, 1’-Biphenyl]-3-carboxylic acid, 2’, 4’-difluoro-4-hydroxy. Its structural formula is:

Molecular Formula:C13H8F2O3

Molecular Weight:250.20 g/mol

Diflunisal, USP is a stable, white, crystalline compound with a melting point of 211° to 213°C. It is practically insoluble in water at neutral or acidic pH. Because it is an organic acid, it dissolves readily in dilute alkali to give a moderately stable solution at room temperature. It is soluble in most organic solvents including ethanol, methanol, and acetone. Each tablet, for oral administration, contains 250 mg and 375 mg diflunisal, USP. In addition, each tablet contains the following inactive ingredients: croscarmellose sodium, FD&C Blue No. 2, hypromellose, microcrystalline cellulose, pregelatinized starch, propylene glycol, sodium stearyl fumarate and titanium dioxide.

CLINICAL PHARMACOLOGY

Action

Dolobid is a non-steroidal drug with analgesic, anti-inflammatory and antipyretic properties. It is a peripherally-acting non-narcotic analgesic drug. Habituation, tolerance, and addiction have not been reported.

Diflunisal is a difluorophenyl derivative of salicylic acid. Chemically, diflunisal differs from aspirin (acetylsalicylic acid) in two respects. The first of these two is the presence of a difluorophenyl substituent at carbon 1. The second difference is the removal of the O-acetyl group from the carbon 4 position. Diflunisal is not metabolized to salicylic acid, and the fluorine atoms are not displaced from the difluorophenyl ring structure.

The precise mechanism of the analgesic and anti-inflammatory actions of diflunisal is not known. Diflunisal is a prostaglandin synthetase inhibitor. In animals, prostaglandins sensitize afferent nerves and potentiate the action of bradykinin in inducing pain. Since prostaglandins are known to be among the mediators of pain and inflammation, the mode of action of diflunisal may be due to a decrease of prostaglandins in peripheral tissues.

Pharmacokinetics and Metabolism

Dolobid is rapidly and completely absorbed following oral administration with peak plasma concentrations occurring between 2 to 3 hours. The drug is excreted in the urine as two soluble glucuronide conjugates accounting for about 90% of the administered dose. Little or no diflunisal is excreted in the feces. Diflunisal appears in human milk in concentrations of 2% to 7% of those in plasma. More than 99% of diflunisal in plasma is bound to proteins.

As is the case with salicylic acid, concentration-dependent pharmacokinetics prevail when Dolobid is administered; a doubling of dosage produces a greater than doubling of drug accumulation. The effect becomes more apparent with repetitive doses. Following single doses, peak plasma concentrations of 41 ± 11 mcg/mL (mean ± S.D.) were observed following 250 mg doses, 87 ± 17 mcg/mL were observed following 500 mg and 124 ± 11 mcg/mL following single 1,000 mg doses. However, following administration of 250 mg b.i.d., a mean peak level of 56 ± 14 mcg/mL was observed on day 8, while the mean peak level after 500 mg b.i.d. for 11 days was 190 ± 33 mcg/mL. In contrast to salicylic acid which has a plasma half-life of 2 1/2 hours, the plasma half-life of diflunisal is 3 to 4 times longer (8 to 12 hours), because of a difluorophenyl substituent at carbon 1. Because of its long half-life and nonlinear pharmacokinetics, several days are required for diflunisal plasma levels to reach steady state following multiple doses. For this reason, an initial loading dose is necessary to shorten the time to reach steady-state levels, and 2 to 3 days of observation are necessary for evaluating changes in treatment regimens if a loading dose is not used.

Studies in baboons to determine passage across the blood-brain barrier have shown that only small quantities of diflunisal, under normal or acidotic conditions are transported into the cerebrospinal fluid (CSF). The ratio of blood/CSF concentrations after intravenous doses of 50 mg/kg or oral doses of 100 mg/kg of diflunisal was 100:1. In contrast, oral doses of 500 mg/kg of aspirin resulted in a blood/CSF ratio of 5:1.

Mild to Moderate Pain

Dolobid is a peripherally-acting analgesic agent with a long duration of action. Dolobid produces significant analgesia within 1 hour and maximum analgesia within 2 to 3 hours.

Consistent with its long half-life, clinical effects of Dolobid mirror its pharmacokinetic behavior, which is the basis for recommending a loading dose when instituting therapy. Patients treated with Dolobid, on the first dose, tend to have a slower onset of pain relief when compared with drugs achieving comparable peak effects. However, Dolobid produces longer lasting responses than the comparative agents.

Comparative single dose clinical studies have established the analgesic efficacy of Dolobid at various dose levels relative to other analgesics. Analgesic effect measurements were derived from hourly evaluations by patients during eight and twelve hour postdosing observation periods. The following information may serve as a guide for prescribing Dolobid.

Dolobid 500 mg was comparable in analgesic efficacy to aspirin 650 mg, acetaminophen 600 mg or 650 mg, and acetaminophen 650 mg with propoxyphene napsylate 100 mg. Patients treated with Dolobid had longer lasting responses than the patients treated with the comparative analgesics.

Dolobid 1,000 mg was comparable in analgesic efficacy to acetaminophen 600 mg with codeine 60 mg. Patients treated with Dolobid had longer lasting responses than the patients who received acetaminophen with codeine.

A loading dose of 1,000 mg provides faster onset of pain relief, shorter time to peak analgesic effect, and greater peak analgesic effect than an initial 500 mg dose.

In contrast to the comparative analgesics, a significantly greater proportion of patients treated with diflunisal did not remedicate and continued to have a good analgesic effect eight to twelve hours after dosing. Seventy-five percent (75%) of patients treated with Dolobid continued to have a good analgesic response at four hours. When patients having a good analgesic response at four hours were followed, 78% of these patients continued to have a good analgesic response at eight hours and 64% at twelve hours.

Chronic Anti-Inflammatory Therapy in Osteoarthritis and Rheumatoid Arthritis

In the controlled, double-blind clinical trials in which Dolobid (500 mg to 1,000 mg a day) was compared with anti-inflammatory doses of aspirin (2 to 4 grams a day), patients treated with Dolobid had a significantly lower incidence of tinnitus and of adverse effects involving the gastrointestinal system than patients treated with aspirin (see also Effect on Fecal Blood Loss).

Osteoarthritis

The effectiveness of Dolobid for the treatment of osteoarthritis was studied in patients with osteoarthritis of the hip and/or knee. The activity of Dolobid was demonstrated by clinical improvement in the signs and symptoms of disease activity.

In a double-blind multicenter study of 12 weeks' duration in which dosages were adjusted according to patient response, Dolobid 500 or 750 mg daily was shown to be comparable in effectiveness to aspirin 2,000 or 3,000 mg daily. In open-label extensions of this study to 24 or 48 weeks, Dolobid continued to show similar effectiveness and generally was well tolerated.

Rheumatoid Arthritis

In controlled clinical trials, the effectiveness of Dolobid was established for both acute exacerbations and long-term management of rheumatoid arthritis. The activity of Dolobid was demonstrated by clinical improvement in the signs and symptoms of disease activity.

In a double-blind multicenter study of 12 weeks' duration in which dosages were adjusted according to patient response, Dolobid 500 or 750 mg daily was comparable in effectiveness to aspirin 2,600 or 3,900 mg daily. In open-label extensions of this study to 52 weeks, Dolobid continued to be effective and was generally well tolerated.

Dolobid 500, 750, or 1,000 mg daily was compared with aspirin 2,000, 3,000, or 4,000 mg daily in a multicenter study of 8 weeks' duration in which dosages were adjusted according to patient response. In this study, Dolobid was comparable in efficacy to aspirin.

In a double-blind multicenter study of 12 weeks' duration in which dosages were adjusted according to patient needs, Dolobid 500 or 750 mg daily and ibuprofen 1,600 or 2,400 mg daily were comparable in effectiveness and tolerability.

In a double-blind multicenter study of 12 weeks' duration, Dolobid 750 mg daily was comparable in efficacy to naproxen 750 mg daily. The incidence of gastrointestinal adverse effects and tinnitus was comparable for both drugs. This study was extended to 48 weeks on an open-label basis. Dolobid continued to be effective and generally well tolerated.

In patients with rheumatoid arthritis, Dolobid and gold salts may be used in combination at their usual dosage levels. In clinical studies, Dolobid added to the regimen of gold salts usually resulted in additional symptomatic relief but did not alter the course of the underlying disease.

Antipyretic Activity

Dolobid is not recommended for use as an antipyretic agent. In single 250 mg, 500 mg, or 750 mg doses, Dolobid produced measurable but not clinically useful decreases in temperature in patients with fever; however, the possibility that it may mask fever in some patients, particularly with chronic or high doses, should be considered.

Uricosuric Effect

In normal volunteers, an increase in the renal clearance of uric acid and a decrease in serum uric acid was observed when Dolobid was administered at 500 mg or 750 mg daily in divided doses. Patients on long-term therapy taking diflunisal at 500 mg to 1,000 mg daily in divided doses showed a prompt and consistent reduction across studies in mean serum uric acid levels, which were lowered as much as 1.4 mg%. It is not known whether Dolobid interferes with the activity of other uricosuric agents.

Effect on Platelet Function

As an inhibitor of prostaglandin synthetase, diflunisal has a dose-related effect on platelet function and bleeding time. In normal volunteers, 250 mg b.i.d. for 8 days had no effect on platelet function, and 500 mg b.i.d., the usual recommended dose, had a slight effect. At 1,000 mg b.i.d., which exceeds the maximum recommended dosage, however, Dolobid inhibited platelet function. In contrast to aspirin, these effects of diflunisal were reversible, because of the absence of the chemically labile and biologically reactive O-acetyl group at the carbon 4 position. Bleeding time was not altered by a dose of 250 mg b.i.d., and was only slightly increased at 500 mg b.i.d. At 1,000 mg b.i.d., a greater increase occurred, but was not statistically significantly different from the change in the placebo group.

Effect on Fecal Blood Loss

When Dolobid was given to normal volunteers at the usual recommended dose of 500 mg twice daily, fecal blood loss was not significantly different from placebo. Aspirin at 1,000 mg four times daily produced the expected increase in fecal blood loss. Dolobid at 1,000 mg twice daily (NOTE: exceeds the recommended dosage) caused a statistically significant increase in fecal blood loss, but this increase was only one-half as large as that associated with aspirin 1,300 mg twice daily.

Effect on Blood Glucose

Dolobid did not affect fasting blood sugar in diabetic patients who were receiving tolbutamide or placebo.

INDICATIONS AND USAGE

Carefully consider the potential benefits and risks of Dolobid and other treatment options before deciding to use Dolobid. Use the lowest effective dose for the shortest duration consistent with individual patient treatment goals (see WARNINGS).

Dolobid is indicated for acute or long-term use for symptomatic treatment of the following:

1. Mild to moderate pain
2. Osteoarthritis
3. Rheumatoid arthritis

CONTRAINDICATIONS

Dolobid is contraindicated in patients with known hypersensitivity to diflunisal or the excipients (see DESCRIPTION).

Dolobid tablets should not be given to patients who have experienced asthma, urticaria, or allergic-type reactions after taking aspirin or other NSAIDs. Severe, rarely fatal, anaphylactic/analphylactoid reactions to NSAIDs have been reported in such patients (see WARNINGS, Anaphylactic/Anaphylactoid Reactionsand PRECAUTIONS, Preexisting Asthma).

In the setting of coronary artery bypass graft (CABG) surgery (see WARNINGS).

WARNINGS

Cardiovascular Effects

Cardiovascular Thrombotic Events

Clinical trials of several COX-2 selective and nonselective NSAIDs of up to three years duration have shown an increased risk of serious cardiovascular (CV) thrombotic events, including myocardial infarction (MI) and stroke, which can be fatal. Based on available data, it is unclear that the risk for CV thrombotic events is similar for all NSAIDs. The relative increase in serious CV thrombotic events over baseline conferred by NSAID use appears to be similar in those with and without known CV disease or risk factors for CV disease. However, patients with known CV disease or risk factors had a higher absolute incidence of excess serious CV thrombotic events, due to their increased baseline rate. Some observational studies found that this increased risk of serious CV thrombotic events began as early as the first weeks of treatment. The increase in CV thrombotic risk has been observed most consistently at higher doses.

To minimize the potential risk for an adverse CV event in NSAID-treated patients, use the lowest effective dose for the shortest duration possible. Physicians and patients should remain alert for the development of such events, throughout the entire treatment course, even in the absence of previous CV symptoms. Patients should be informed about the symptoms of serious CV events and the steps to take if they occur.

There is no consistent evidence that concurrent use of aspirin mitigates the increased risk of serious CV thrombotic events associated with NSAID use. The concurrent use of aspirin and an NSAID, such as Dolobid, increases the risk of serious gastrointestinal (GI) events (see
WARNINGS).

Status Post Coronary Artery Bypass Graft (CABG) Surgery

Two large, controlled clinical trials of a COX-2 selective NSAID for the treatment of pain in the first 10 to 14 days following CABG surgery found an increased incidence of myocardial infarction and stroke. NSAIDs are contraindicated in the setting of CABG (see CONTRAINDICATIONS).

Post-MI Patients

Observational studies conducted in the Danish National Registry have demonstrated that patients treated with NSAIDs in the post-MI period were at increased risk of reinfarction, CV-related death, and all-cause mortality beginning in the first week of treatment. In this same cohort, the incidence of death in the first year post MI was 20 per 100 person years in NSAID-treated patients compared to 12 per 100 person years in non-NSAID exposed patients. Although the absolute rate of death declined somewhat after the first year post-MI, the increased relative risk of death in NSAID users persisted over at least the next four years of follow-up.

Avoid the use of Dolobid in patients with a recent MI unless the benefits are expected to outweigh the risk of recurrent CV thrombotic events. If diflunisal tablets is used in patients with a recent MI, monitor patients for signs of cardiac ischemia.

Hypertension

NSAIDs, including Dolobid, can lead to onset of new hypertension or worsening of preexisting hypertension, either of which may contribute to the increased incidence of CV events. Patients taking thiazides or loop diuretics may have impaired response to these therapies when taking NSAIDs. NSAIDs, including Dolobid should be used with caution in patients with hypertension. Blood pressure (BP) should be monitored closely during the initiation of NSAID treatment and throughout the course of therapy.

Heart Failure and Edema

The Coxib and traditional NSAID Trialists’ Collaboration meta-analysis of randomized controlled trials demonstrated an approximately two-fold increase in hospitalizations for heart failure in COX-2 selective-treated patients and nonselective NSAID-treated patients compared to placebo-treated patients. In a Danish National Registry study of patients with heart failure, NSAID use increased the risk of MI, hospitalization for heart failure, and death.

Additionally, fluid retention and edema have been observed in some patients treated with NSAIDs. Use of Dolobid may blunt the CV effects of several therapeutic agents used to treat these medical conditions [e.g., diuretics, ACE inhibitors, or angiotensin receptor blockers (ARBs)] (see Drug Interactions).

Avoid the use of Dolobid in patients with severe heart failure unless the benefits are expected to outweigh the risk of worsening heart failure. If Dolobid is used in patients with severe heart failure, monitor patients for signs of worsening heart failure.

Gastrointestinal Effects – Risk of Ulceration, Bleeding and Perforation

NSAIDs, including Dolobid, can cause serious gastrointestinal (GI) adverse events including inflammation, bleeding, ulceration, and perforation of the stomach, small intestine, or large intestine, which can be fatal. These serious adverse events can occur at any time, with or without warning symptoms, in patients treated with NSAIDs. Only one in five patients, who develop a serious upper GI adverse event on NSAID therapy, is symptomatic. Upper GI ulcers, gross bleeding, or perforation caused by NSAIDs occur in approximately 1% of patients treated for 3 to 6 months, and in about 2% to 4% of patients treated for one year. These trends continue with longer duration of use, increasing the likelihood of developing a serious GI event at some time during the course of therapy. However, even short-term therapy is not without risk.

NSAIDs should be prescribed with extreme caution in those with a prior history of ulcer disease or gastrointestinal bleeding. Patients with a prior history of peptic ulcer disease and/or gastrointestinal bleedingwho use NSAIDs have a greater than 10 fold increased risk for developing a GI bleed compared to patients with neither of these risk factors. Other factors that increase the risk for GI bleeding in patients treated with NSAIDs include concomitant use of oral corticosteroids or anticoagulants, longer duration of NSAID therapy, smoking, use of alcohol, older age, and poor general health status. Most spontaneous reports of fatal GI events are in elderly or debilitated patients and therefore, special care should be taken in treating this population.

To minimize the potential risk for an adverse GI event in patients treated with an NSAID, the lowest effective dose should be used for the shortest possible duration. Patients and physicians should remain alert for signs and symptoms of GI ulceration and bleeding during NSAID therapy and promptly initiate additional evaluation and treatment if a serious GI adverse event is suspected. This should include discontinuation of the NSAID until a serious GI adverse event is ruled out. For high risk patients, alternate therapies that do not involve NSAIDs should be considered.

Renal Effects

Long-term administration of NSAIDs has resulted in renal papillary necrosis and other renal injury. Renal toxicity has also been seen in patients in whom renal prostaglandins have a compensatory role in the maintenance of renal perfusion. In these patients, administration of a non-steroidal anti-inflammatory drug may cause a dose-dependent reduction in prostaglandin formation and, secondarily, in renal blood flow, which may precipitate overt renal decompensation. Patients at greatest risk of this reaction are those with impaired renal function, heart failure, liver dysfunction, those taking diuretics and ACE inhibitors, patients who are volume depleted, and the elderly. Discontinuation of NSAID therapy is usually followed by recovery to the pretreatment state.

Advanced Renal Disease

No information is available from controlled clinical studies regarding the use of Dolobid in patients with advanced renal disease. Therefore, treatment with Dolobid is not recommended in these patients with advanced renal disease. If Dolobid therapy must be initiated, close monitoring of the patient's renal function is advisable.

Anaphylactic/Anaphylactoid Reactions

As with other NSAIDs, anaphylactic/anaphylactoid reactions may occur in patients without known prior exposure to Dolobid. Dolobid should not be given to patients with the aspirin triad. This symptom complex typically occurs in asthmatic patients who experience rhinitis with or without nasal polyps, or who exhibit severe, potentially fatal bronchospasm after taking aspirin or other NSAIDs (see CONTRAINDICATIONSand PRECAUTIONS, Preexisting Asthma). Emergency help should be sought in cases where an anaphylactic/ anaphylactoid reaction occurs.

Serious Skin Reactions

NSAIDs, including diflunisal, can cause serious skin adverse reactions such as exfoliative dermatitis, Stevens-Johnson Syndrome (SJS), and toxic epidermal necrolysis (TEN), which can be fatal. NSAIDs can also cause fixed drug eruption (FDE). FDE may present as a more severe variant known as generalized bullous fixed drug eruption (GBFDE), which can be life-threatening. These serious events may occur without warning. Inform patients about the signs and symptoms of serious skin reactions, and to discontinue the use of Dolobid at the first appearance of skin rash or any other sign of hypersensitivity. Dolobid is contraindicated in patients with previous serious skin reactions to NSAIDs (see CONTRAINDICATIONS)

Drug Reaction with Eosinophilia and Systemic Symptoms (DRESS) has been reported in patients taking NSAIDs such as Dolobid. Some of these events have been fatal or life-threatening. DRESS typically, although not exclusively, presents with fever, rash, lymphadenopathy, and/or facial swelling. Other clinical manifestations may include hepatitis, nephritis, hematological abnormalities, myocarditis, or myositis. Sometimes symptoms of DRESS may resemble an acute viral infection. Eosinophilia is often present. Because this disorder is variable in its presentation, other organ systems not noted here may be involved. It is important to note that early manifestations of hypersensitivity, such as fever or lymphadenopathy, may be present even though rash is not evident. If such signs or symptoms are present, discontinue Dolobid and evaluate the patient immediately.

Hypersensitivity Syndrome

A potentially life-threatening, apparent hypersensitivity syndrome has been reported. This multisystem syndrome includes constitutional symptoms (fever, chills), and cutaneous findings (see ADVERSE REACTIONS, Dermatologic). It may also include involvement of major organs (changes in liver function, jaundice, leukopenia, thrombocytopenia, eosinophilia, disseminated intravascular coagulation, renal impairment, including renal failure), and less specific findings (adenitis, arthralgia, myalgia, arthritis, malaise, anorexia, disorientation). If evidence of hypersensitivity occurs, therapy with Dolobid should be discontinued.

Fetal Toxicity

Premature Closure of Fetal Ductus Arteriosus:

Avoid use of NSAIDs, including Dolobid, in pregnant women at about 30 weeks gestation and later. NSAIDs including Dolobid, increase the risk of premature closure of the fetal ductus arteriosus at approximately this gestational age.

Oligohydramnios/Neonatal Renal Impairment:

Use of NSAIDs, including Dolobid, at about 20 weeks gestation or later in pregnancy may cause fetal renal dysfunction leading to oligohydramnios and, in some cases, neonatal renal impairment. These adverse outcomes are seen, on average, after days to weeks of treatment, although oligohydramnios has been infrequently reported as soon as 48 hours after NSAID initiation. Oligohydramnios is often, but not always, reversible with treatment discontinuation. Complications of prolonged oligohydramnios may, for example, include limb contractures and delayed lung maturation. In some postmarketing cases of impaired neonatal renal function, invasive procedures such as exchange transfusion or dialysis were required.

If NSAID treatment is necessary between about 20 weeks and 30 weeks gestation, limit Dolobid, use to the lowest effective dose and shortest duration possible. Consider ultrasound monitoring of amniotic fluid if Dolobid treatment extends beyond 48 hours. Discontinue Dolobid if oligohydramnios occurs and follow up according to clinical practice [see PRECAUTIONS; Pregnancy] .

PRECAUTIONS

General

Dolobid cannot be expected to substitute for corticosteroids or to treat corticosteroid insufficiency. Abrupt discontinuation of corticosteroids may lead to disease exacerbation. Patients on prolonged corticosteroid therapy should have their therapy tapered slowly if a decision is made to discontinue corticosteroids.

The pharmacological activity of Dolobid in reducing fever and inflammation may diminish the utility of these diagnostic signs in detecting complications of presumed noninfectious, painful conditions.

Hepatic Effects

Borderline elevations of one or more liver tests may occur in up to 15% of patients taking NSAIDs including Dolobid. These laboratory abnormalities may progress, may remain unchanged, or may be transient with continuing therapy. Notable elevations of ALT or AST (approximately three or more times the upper limit of normal) have been reported in approximately 1% of patients in clinical trials with NSAIDs. In addition, rare cases of severe hepatic reactions, including jaundice and fatal fulminant hepatitis, liver necrosis and hepatic failure, some of them with fatal outcomes have been reported.

A patient with symptoms and/or signs suggesting liver dysfunction, or in whom an abnormal liver test has occurred, should be evaluated for evidence of the development of a more severe hepatic reaction while on therapy with Dolobid . If clinical signs and symptoms consistent with liver disease develop, or if systemic manifestations occur (e.g., eosinophilia, rash, etc.), Dolobid should be discontinued.

Hematological Effects

Anemia is sometimes seen in patients receiving NSAIDs, including Dolobid. This may be due to fluid retention, occult or gross GI blood loss, or an incompletely described effect upon erythropoiesis. Patients on long-term treatment with NSAIDs, including Dolobid, should have their hemoglobin or hematocrit checked if they exhibit any signs or symptoms of anemia.

NSAIDs inhibit platelet aggregation and have been shown to prolong bleeding time in some patients. Unlike aspirin, their effect on platelet function is quantitatively less, of shorter duration, and reversible. Patients receiving diflunisal tablets who may be adversely affected by alterations in platelet function, such as those with coagulation disorders or patients receiving anticoagulants, should be carefully monitored.

Preexisting Asthma

Patients with asthma may have aspirin-sensitive asthma. The use of aspirin in patients with aspirin-sensitive asthma has been associated with severe bronchospasm which can be fatal. Since cross reactivity, including bronchospasm, between aspirin and other non-steroidal anti-inflammatory drugs has been reported in such aspirin-sensitive patients, diflunisal tablets should not be administered to patients with this form of aspirin sensitivity and should be used with caution in patients with preexisting asthma.

Ocular Effects

Because of reports of adverse eye findings with agents of this class, it is recommended that patients who develop eye complaints during treatment with Dolobid have ophthalmologic studies.

Reye’s Syndrome

Acetylsalicylic acid has been associated with Reye’s syndrome. Because Dolobid is a derivative of salicylic acid, the possibility of its association with Reye’s syndrome cannot be excluded.

Information for Patients

Patients should be informed of the following information before initiating therapy with an NSAID and periodically during the course of ongoing therapy. Patients should also be encouraged to read the NSAID Medication Guide that accompanies each prescription dispensed.

Cardiovascular Thrombotic Events

Advise patients to be alert for the symptoms of cardiovascular thrombotic events, including chest pain, shortness of breath, weakness, or slurring of speech, and to report any of these symptoms to their health care provider immediately (see WARNINGS).

Gastrointestinal Bleeding, Ulceration, and Perforation

Dolobid tablets, like other NSAIDs, can cause GI discomfort and, rarely, serious GI side effects, such as ulcers and bleeding, which may result in hospitalization and even death. Although serious GI tract ulcerations and bleeding can occur without warning symptoms, patients should be alert for the signs and symptoms of ulcerations and bleeding, and should ask for medical advice when observing any indicative signs or symptoms including epigastric pain, dyspepsia, melena, and hematemesis. Patients should be apprised of the importance of this follow-up (see WARNINGS, Gastrointestinal Effects - Risk of Ulceration, Bleeding, and Perforation).

Serious Skin Reactions, including DRESS

Advise patients to stop taking Dolobid immediately if they develop any type of rash or fever and to contact their healthcare provider as soon as possible (see WARNINGS).

Heart Failure And Edema

Advise patients to be alert for the symptoms of congestive heart failure including shortness of breath, unexplained weight gain, or edema and to contact their healthcare provider if such symptoms occur (see WARNINGS).

Hepatotoxicity

Patients should be informed of the warning signs and symptoms of hepatotoxicity (e.g., nausea, fatigue, lethargy, pruritus, jaundice, right upper quadrant tenderness, and "flu-like" symptoms). If these occur, patients should be instructed to stop therapy and seek immediate medical therapy.

Anaphylactic Reactions

Patients should be informed of the signs of an anaphylactic/anaphylactoid reaction (e.g., difficulty breathing, swelling of the face or throat). If these occur, patients should be instructed to seek immediate emergency help (see WARNINGS).

Fetal Toxicity

Inform pregnant women to avoid use of Dolobid and other NSAIDs starting at 30 weeks gestation because of the risk of the premature closing of the fetal ductus arteriosus. If treatment with Dolobid is needed for a pregnant woman between about 20 to 30 weeks gestation, advise her that she may need to be monitored for oligohydramnios, if treatment continues for longer than 48 hours (see WARNINGS; Fetal Toxicity, PRECAUTIONS; Pregnancy) .

Laboratory Tests

Because serious GI tract ulcerations and bleeding can occur without warning symptoms, physicians should monitor for signs or symptoms of GI bleeding. Patients on long-term treatment with NSAIDs, should have their CBC and a chemistry profile checked periodically. If clinical signs and symptoms consistent with liver or renal disease develop, systemic manifestations occur (e.g., eosinophilia, rash, etc.) or if abnormal liver tests persist or worsen, Dolobid should be discontinued.

Drug Interactions

ACE-inhibitors and Angiotensin II Anagonists

Reports suggest that NSAIDs may diminish the antihypertensive effect of ACE-inhibitors and angiotensin II antagonists. These interactions should be given consideration in patients taking NSAIDs concomitantly with ACE-inhibitors or angiotensin II antagonists. In some patients with compromised renal function, the co-administration of an NSAID and an ACE-inhibitor or an angiotensin II antagonist may result in further deterioration of renal function, including possible acute renal failure, which is usually reversible.

Acetaminophen

In normal volunteers, concomitant administration of Dolobid and acetaminophen resulted in an approximate 50% increase in plasma levels of acetaminophen. Acetaminophen had no effect on plasma levels of. Dolobid. Since acetaminophen in high doses has been associated with hepatotoxicity, concomitant administration of Dolobid tablets and acetaminophen should be used cautiously, with careful monitoring of patients.

Concomitant administration of Dolobid and acetaminophen in dogs, but not in rats, at approximately 2 times the recommended maximum human therapeutic dose of each (40 to 52 mg/kg/day of Dolobid/acetaminophen), resulted in greater gastrointestinal toxicity than when either drug was administered alone. The clinical significance of these findings has not been established.

Antacids

Concomitant administration of antacids may reduce plasma levels of Dolobid. This effect is small with occasional doses of antacids, but may be clinically significant when antacids are used on a continuous schedule.

Aspirin

When Dolobid is administered with aspirin, its protein binding is reduced, although the clearance of free diflunisal is not altered. The clinical significance of this interaction is not known; however, as with other NSAIDs, concomitant administration of diflunisal and aspirin is not generally recommended because of the potential of increased adverse effects.

In normal volunteers, a small decrease in Dolobid levels was observed when multiple doses of Dolobid and aspirin were administered concomitantly.

Cyclosporine

Administration of non-steroidal anti-inflammatory drugs concomitantly with cyclosporine has been associated with an increase in cyclosporine-induced toxicity, possibly due to decreased synthesis of renal prostacyclin. NSAIDs should be used with caution in patients taking cyclosporine, and renal function should be carefully monitored.

Diuretics

Clinical studies, as well as postmarketing observations, have shown that Dolobid can reduce the natriuretic effect of furosemide and thiazides in some patients. This response has been attributed to inhibition of renal prostaglandin synthesis.

In normal volunteers, concomitant administration of Dolobid and hydrochlorothiazide resulted in significantly.increased plasma levels of hydrochlorothiazide. Dolobid decreased the hyperuricemic effect of hydrochlorothiazide. During concomitant therapy with NSAIDs, the patient should be observed closely for signs of renal failure (see WARNINGS, Renal Effects), as well as to assure diuretic efficacy.

Lithium

NSAIDs have produced an elevation of plasma lithium levels and a reduction in renal lithium clearance. The mean minimum lithium concentration increased 15% and the renal clearance was decreased by approximately 20%. These effects have been attributed to inhibition of renal prostaglandin synthesis by the NSAID. Thus, when NSAIDs and lithium are administered concurrently, subjects should be observed carefully for signs of lithium toxicity.

Methotrexate

NSAIDs have been reported to competitively inhibit methotrexate accumulation in rabbit kidney slices. This may indicate that they could enhance the toxicity of methotrexate. Caution should be used when NSAIDs are administered concomitantly with methotrexate.

NSAIDs

The administration of Dolobid to normal volunteers receiving indomethacin decreased the renal clearance and significantly increased the plasma levels of indomethacin. In some patients the combined use of indomethacin and Dolobid has been associated with fatal gastrointestinal hemorrhage. Therefore, indomethacin and Dolobid tablets should not be used concomitantly.

The concomitant use of Dolobid tablets and other NSAIDs is not recommended due to the increased possibility of gastrointestinal toxicity, with little or no increase in efficacy. The following information was obtained from studies in normal volunteers.

Sulindac

The concomitant administration of diflunisal and sulindac in normal volunteers resulted in lowering of the plasma levels of the active sulindac sulfide metabolite by approximately one-third.

Naproxen

The concomitant administration of Dolobid and naproxen in normal volunteers had no effect on the plasma levels of naproxen, but significantly decreased the urinary excretion of naproxen and its glucuronide metabolite. Naproxen had no effect on plasma levels of Dolobid.

Oral Anticoagulants

In some normal volunteers, the concomitant administration of diflunisal and warfarin, acenocoumarol, or phenprocoumon resulted in prolongation of prothrombin time. This may occur because diflunisal competitively displaces coumarins from protein binding sites. Accordingly, when Dolobid tablets are administered with oral anticoagulants, the prothrombin time should be closely monitored during and for several days after concomitant drug administration. Adjustment of dosage of oral anticoagulants may be required. The effects of warfarin and NSAIDs on GI bleeding are synergistic, such that users of both drugs together have a risk of serious GI bleeding higher than users of either drug alone.

Tolbutamide

In diabetic patients receiving Dolobid and tolbutamide, no significant effects were seen on tolbutamide plasma levels or fasting blood glucose.

Drug/Laboratory Test Interactions

Serum Salicylate Assays

Caution should be used in interpreting the results of serum salicylate assays when diflunisal is present. Salicylate levels have been found to be falsely elevated with some assay methods.

Carcinogenesis, Mutagenesis, Impairment of Fertility

Diflunisal did not affect the type or incidence of neoplasia in a 105 week study in the rat given doses up to 40 mg/kg/day (equivalent to approximately 1.3 times the maximum recommended human dose), or in long-term carcinogenic studies in mice given diflunisal at doses up to 80 mg/kg/day (equivalent to approximately 2.7 times the maximum recommended human dose). It was concluded that there was no carcinogenic potential for diflunisal.

Diflunisal passes the placental barrier to a minor degree in the rat. Diflunisal had no mutagenic activity after oral administration in the dominant lethal assay, in the Ames microbial mutagen test or in the V-79 Chinese hamster lung cell assay.

No evidence of impaired fertility was found in reproduction studies in rats at doses up to 50 mg/kg/day.

Pregnancy

Risk Summary

Use of NSAIDs, including Dolobid can cause premature closure of the fetal ductus arteriosus and fetal renal dysfunction leading to oligohydramnios and, in some cases, neonatal renal impairment. Because of these risks, limit dose and duration of diflunisal tablets use between about 20 and 30 weeks of gestation, and avoid Dolobid use at about 30 weeks of gestation and later in pregnancy (see WARNINGS; Fetal Toxicity).

Premature Closure of Fetal Ductus Arteriosus

Use of NSAIDs, including Dolobid at about 30 weeks gestation or later in pregnancy increases the risk of premature closure of the fetal ductus arteriosus.

Oligohydramnios/Neonatal Renal Impairment

Use of NSAIDs at about 20 weeks gestation or later in pregnancy has been associated with cases of fetal renal dysfunction leading to oligohydramnios, and in some cases, neonatal renal impairment.

Data from observational studies regarding other potential embryofetal risks of NSAID use in women in the first or second trimesters of pregnancy are inconclusive. Based on animal data, prostaglandins have been shown to have an important role in endometrial vascular permeability, blastocyst implantation, and decidualization. In animal studies, administration of prostaglandin synthesis inhibitors such as Dolobid, resulted in increased pre- and post-implantation loss. Prostaglandins also have been shown to have an important role in fetal kidney development. In published animal studies, prostaglandin synthesis inhibitors have been reported to impair kidney development when administered at clinically relevant doses.

The estimated background risk of major birth defects and miscarriage for the indicated population(s) is unknown. All pregnancies have a background risk of birth defect, loss, or other adverse outcomes. In the U.S. general population, the estimated background risk of major birth defects and miscarriage in clinically recognized pregnancies is 2% to 4% and 15% to 20%, respectively.

Clinical Considerations

Fetal/Neonatal Adverse Reactions

Premature Closure of Fetal Ductus Arteriosus:

Avoid use of NSAIDs in women at about 30 weeks gestation and later in pregnancy, because NSAIDs, including Dolobid , can cause premature closure of the fetal ductus arteriosus (see WARNINGS; Fetal Toxicity).

Oligohydramnios/Neonatal Renal Impairment

If an NSAID is necessary at about 20 weeks gestation or later in pregnancy, limit the use to the lowest effective dose and shortest duration possible. If Dolobid treatment extends beyond 48 hours, consider monitoring with ultrasound for oligohydramnios. If oligohydramnios occurs, discontinue diflunisal tablets and follow up according to clinical practice (see WARNINGS; Fetal Toxicity).

Data

Human Data

Premature Closure of Fetal Ductus Arteriosus:

Published literature reports that the use of NSAIDs at about 30 weeks of gestation and later in pregnancy may cause premature closure of the fetal ductus arteriosus.

Oligohydramnios/Neonatal Renal Impairment:

Published studies and postmarketing reports describe maternal NSAID use at about 20 weeks gestation or later in pregnancy associated with fetal renal dysfunction leading to oligohydramnios, and in some cases, neonatal renal impairment. These adverse outcomes are seen, on average, after days to weeks of treatment, although oligohydramnios has been infrequently reported as soon as 48 hours after NSAID initiation. In many cases, but not all, the decrease in amniotic fluid was transient and reversible with cessation of the drug. There have been a limited number of case reports of maternal NSAID use and neonatal renal dysfunction without oligohydramnios, some of which were irreversible. Some cases of neonatal renal dysfunction required treatment with invasive procedures, such as exchange transfusion or dialysis.

Methodological limitations of these postmarketing studies and reports include lack of a control group; limited information regarding dose, duration, and timing of drug exposure; and concomitant use of other medications. These limitations preclude establishing a reliable estimate of the risk of adverse fetal and neonatal outcomes with maternal NSAID use. Because the published safety data on neonatal outcomes involved mostly preterm infants, the generalizability of certain reported risks to the full-term infant exposed to NSAIDs through maternal use is uncertain.

Animal Data

A dose of 60 mg/kg/day of diflunisal (equivalent to two times the maximum human dose) was maternotoxic, embryotoxic, and teratogenic in rabbits. In three of six studies in rabbits, evidence of teratogenicity was observed at doses ranging from 40 to 50 mg/kg/day. Teratology studies in mice, at doses up to 45 mg/kg/day, and in rats at doses up to 100 mg/kg/day, revealed no harm to the fetus due to diflunisal. Aspirin and other salicylates have been shown to be teratogenic in a wide variety of species, including the rat and rabbit, at doses ranging from 50 to 400 mg/kg/day (approximately one to eight times the human dose). Animal reproduction studies are not always predictive of human response. There are no adequate and well controlled studies with diflunisal in pregnant women. Dolobid should be used in pregnancy only if the potential benefit justifies the potential risk to the fetus.

Labor and Delivery

In rat studies with NSAIDs, as with other drugs known to inhibit prostaglandin synthesis, an increased incidence of dystocia, delayed parturition, and decreased pup survival occurred. The effects of Dolobid on labor and delivery in pregnant women are unknown.

Nursing Mothers

Dolobid is excreted in human milk in concentrations of 2% to 7% of those in plasma. Because of the potential for serious adverse reactions in nursing infants from Dolobid, a decision should be made whether to discontinue nursing or to discontinue the drug, taking into account the importance of the drug to the mother.

Pediatric Use

Safety and effectiveness of Dolobid in pediatric patients below the age of 12 have not been established. Use of Dolobid in pediatric patients below the age of 12 is not recommended.

The adverse effects observed following diflunisal administration to neonatal animals appear to be species, age, and dose-dependent. At dose levels approximately 3 times the usual human therapeutic dose, both aspirin (200 to 400 mg/kg/day) and diflunisal (80 mg/kg/day) resulted in death, leukocytosis, weight loss, and bilateral cataracts in neonatal (4 to 5-day-old) beagle puppies after 2 to 10 doses. Administration of an 80 mg/kg/day dose of diflunisal to 25-day-old puppies resulted in lower mortality, and did not produce cataracts. In newborn rats, a 400 mg/kg/day dose of aspirin resulted in increased mortality and some cataracts, whereas the effects of diflunisal administration at doses up to 140 mg/kg/day were limited to a decrease in average body weight gain.

Geriatric Use

As with any NSAID, caution should be exercised in treating the elderly (65 years and older) since advancing age appears to increase the possibility of adverse reactions. Elderly patients seem to tolerate ulceration or bleeding less well than other individuals and many spontaneous reports of fatal GI events are in this population (see WARNINGS, Gastrointestinal Effects – Risk of Ulceration, Bleeding, and Perforation).

This drug is known to be substantially excreted by the kidney and the risk of toxic reactions to this drug may be greater in patients with impaired renal function. Because elderly patients are more likely to have decreased renal function, care should be taken in dose selection and it may be useful to monitor renal function (see WARNINGS, Renal Effects).

ADVERSE REACTIONS

The adverse reactions observed in controlled clinical trials encompass observations in 2,427 patients.

Listed below are the adverse reactions reported in the 1,314 of these patients who received treatment in studies of two weeks or longer. Five hundred thirteen patients were treated for at least 24 weeks, 255 patients were treated for at least 48 weeks, and 46 patients were treated for 96 weeks. In general, the adverse reactions listed below were 2 to 14 times less frequent in the 1,113 patients who received short-term treatment for mild to moderate pain.

Incidence Greater Than 1%

Gastrointestinal

The most frequent types of adverse reactions occurring with diflunisal are gastrointestinal: these include nausea*, vomiting, dyspepsia*, gastrointestinal pain*, diarrhea*, constipation, and flatulence.

Psychiatric

Somnolence, insomnia.

Central Nervous System

Dizziness.

Special Senses

Tinnitus.

Dermatologic

Rash*.

Miscellaneous

Headache*, fatigue/tiredness.

* Incidence between 3% and 9%. Those reactions occurring in 1% to 3% are not marked with an asterisk.

Skin and Appendages:

Exfoliative dermatitis, Stevens-Johnson Syndrome (SJS), toxic epidermal necrolysis (TEN), and can fixed drug reaction (FDE)

Incidence Less Than 1 in 100

The following adverse reactions, occurring less frequently than 1 in 100, were reported in clinical trials or since the drug was marketed. The probability exists of a causal relationship between diflunisal and these adverse reactions.

Dermatologic

Erythema multiforme, exfoliative dermatitis, Stevens-Johnson Syndrome (SJS), toxic epidermal necrolysis (TEN), and fixed drug eruption (FDE), urticaria, pruritus, sweating, dry mucous membranes, stomatitis, photosensitivity.

Gastrointestinal

Peptic ulcer, gastrointestinal bleeding, anorexia, eructation, gastrointestinal perforation, gastritis. Liver function abnormalities; jaundice, sometimes with fever; cholestasis; hepatitis.

Hematologic

Thrombocytopenia; agranulocytosis; hemolytic anemia.

Genitourinary

Dysuria; renal impairment, including renal failure; interstitial nephritis; hematuria; proteinuria.

Psychiatric

Nervousness, depression, hallucinations, confusion, disorientation.

Central Nervous System

Vertigo; light-headedness; paresthesias.

Special Senses

Transient visual disturbances including blurred vision.

Hypersensitivity Reactions

Acute anaphylactic reaction with bronchospasm; angioedema; flushing. Hypersensitivity vasculitis. Hypersensitivity syndrome (see PRECAUTIONS).

Miscellaneous

Asthenia, edema.

Causal Relationship Unknown

Other reactions have been reported in clinical trials or since the drug was marketed, but occurred under circumstances where a causal relationship could not be established. However, in these rarely reported events, that possibility cannot be excluded. Therefore, these observations are listed to serve as alerting information to physicians.

Respiratory

Dyspnea.

Cardiovascular

Palpitation, syncope.

Musculoskeletal

Muscle cramps.

Genitourinary

Nephrotic syndrome.

Special Senses

Hearing loss.

Miscellaneous

Chest pain.

A rare occurrence of fulminant necrotizing fasciitis, particularly in association with Group A β-hemolytic streptococcus, has been described in persons treated with non-steroidal anti-inflammatory agents, including diflunisal, sometimes with fatal outcome (see also PRECAUTIONS, General).

Potential Adverse Effects

In addition, a variety of adverse effects not observed with diflunisal in clinical trials or in marketing experience but reported with other non-steroidal analgesic/anti-inflammatory agents should be considered potential adverse effects of Dolobid.

To report SUSPECTED ADVERSE REACTIONS, contact INA Pharmaceutics, Inc. at 866-835-0469. or FDA at 1-800-FDA-1088 orwww.fda.gov/medwatch.

OVERDOSAGE

Cases of overdosage have occurred and deaths have been reported. Most patients recovered without evidence of permanent sequelae. The most common signs and symptoms observed with overdosage were drowsiness, vomiting, nausea, diarrhea, hyperventilation, tachycardia, sweating, tinnitus, disorientation, stupor, and coma. Diminished urine output and cardiorespiratory arrest have also been reported. The lowest dosage of diflunisal at which a death has been reported was 15 grams without the presence of other drugs. In a mixed drug overdose, ingestion of 7.5 grams of diflunisal resulted in death.

In the event of overdosage, the stomach should be emptied by inducing vomiting or by gastric lavage, and the patient carefully observed and given symptomatic and supportive treatment. Because of the high degree of protein binding, hemodialysis may not be effective.

The oral LD50of the drug is 500 mg/kg and 826 mg/kg in female mice and female rats, respectively.

DOSAGE AND ADMINISTRATION

Carefully consider the potential benefits and risks of Dolobid and other treatment options before deciding to use Dolobid. Use the lowest effective dose for the shortest duration consistent with individual patient treatment goals (see WARNINGS).

After observing the response to initial therapy with Dolobid, the dose and frequency should be adjusted to suit an individual patient's needs.

Concentration-dependent pharmacokinetics prevail when Dolobid is administered; a doubling of dosage produces a greater than doubling of drug accumulation. The effect becomes more apparent with repetitive doses.

For mild to moderate pain, an initial dose of 1,000 mg followed by 500 mg every 12 hours is recommended for most patients. Following the initial dose, some patients may require 500 mg every 8 hours.

A lower dosage may be appropriate depending on such factors as pain severity, patient response, weight, or advanced age; for example, 500 mg initially, followed by 250 mg every 8 to 12 hours.

For osteoarthritis and rheumatoid arthritis, the suggested dosage range is 500 mg to 1,000 mg daily in two divided doses. The dosage of Dolobid may be increased or decreased according to patient response.

Maintenance doses higher than 1,500 mg a day are not recommended.

Tablets should be swallowed whole, not crushed or chewed.

HOW SUPPLIED

Dolobid is supplied as follows:

250 mg tablets: Modified Capsule Shape, Blue Film Coated Tablets, Debossed “250” on One Side and Plain on the Reverse Side.

Bottles of 60: NDC 74157-009-60

375 mg tablets: Modified Capsule Shape, Blue Film Coated Tablets, Debossed “375” on One Side and Plain on the Reverse Side

Bottles of 60: NDC 74157-101-60

Dispense in a well-closed container as defined in the USP, with a child-resistant closure (as required).

Keep tightly closed.

Store at 20° to 25°C (68° to 77°F); excursions permitted between 15° to 30°C (59° to 86°F) [see USP Controlled Room Temperature].

Manufactured for:

INA Pharmaceutics Inc.

Fairmont, WV 26554

Revised: 06/2024

MEDICATION GUIDE

Medication Guide for Nonsteroidal Anti-Inflammatory Drugs (NSAIDs)

What is the most important information I should know about medicines called Nonsteroidal Anti-Inflammatory Drugs (NSAIDs)?

NSAIDs can cause serious side effects, including:

- Increased risk of a heart attack or stroke that can lead to death.This risk may happen early in treatment and may increase:

ο with increasing doses of NSAIDs

o with longer use of NSAIDs

Do not take NSAIDs right before or after a heart surgery called a “coronary artery bypass graft (CABG)."

Avoid taking NSAIDs after a recent heart attack, unless your healthcare provider tells you to. You may have an increased risk of another heart attack if you take NSAIDs after a recent heart attack.

- Increased risk of bleeding, ulcers, and tears (perforation) of the esophagus (tube leading from the mouth to the stomach), stomach and intestines:

o anytime during use
o without warning symptoms
o that may cause death

The risk of getting an ulcer or bleeding increases with:

o past history of stomach ulcers, or stomach or intestinal bleeding with use of NSAIDs

o taking medicines called “corticosteroids”, “anticoagulants”, “SSRIs”, or “SNRIs”

o increasing doses of NSAIDs

o longer use of NSAIDs

o smoking

o drinking alcohol

o older age

o poor health

o advanced liver disease

o bleeding problems

NSAIDs should only be used:

o exactly as prescribed

o at the lowest dose possible for your treatment

o for the shortest time needed

What are NSAIDs?

NSAIDs are used to treat pain and redness, swelling, and heat (inflammation) from medical conditions such as different types of arthritis, menstrual cramps, and other types of short-term pain.

Who should not take a NSAIDs?

Do not take NSAIDs:

- if you have had an asthma attack, hives, or other allergic reaction with aspirin or any other NSAIDs.
- Right before or after heart bypass surgery.

Before taking NSAIDS, tell your healthcare provider about all of your medical conditions, including if you:

- have liver or kidney problems
- have high blood pressure
- have asthma
- are pregnant or plan to become pregnant. Taking NSAIDs at about 20 weeks of pregnancy or later may harm your unborn baby. If you need to take NSAIDs for more than 2 days when you are between 20 and 30 weeks of pregnancy, your healthcare provider may need to monitor the amount of fluid in your womb around your baby. You should not take NSAIDs after about 30 weeks of pregnancy.
- are breastfeeding or plan to breast feed.

Tell your healthcare provider about all of the medicines you take, including prescription or over-the-counter medicines, vitamins or herbal supplements.NSAIDs and some other medicines can interact with each other and cause serious side effects. Do not start taking any new medicine without talking to your healthcare provider first.

What are the possible side effects of NSAIDs?

NSAIDs can cause serious side effects, including:

See “What is the most important information I should know about medicines called Nonsteroidal Anti-inflammatory Drugs (NSAIDs)?

- new or worse high blood pressure
- heart failure
- liver problems including liver failure
- kidney problems including kidney failure
- low red blood cells (anemia)
- life-threatening skin reactions
- life threatening allergic reactions
- Other side effects of NSAIDs include:stomach pain, constipation, diarrhea, gas, heartburn, nausea, vomiting, and dizziness.

Get emergency help right away if you get any of the following symptoms:

- shortness of breath or trouble breathing
- chest pain
- weakness in one part or side of your body
- slurred speech
- swelling of the face or throat

Stop taking your NSAID and call your healthcare provider right away if you get any of the following symptoms:

- nausea
- more tired or weaker than usual
- diarrhea
- itching
- your skin or eyes look yellow
- indigestion or stomach pain
- flu-like symptoms
- vomit blood
- there is blood in your bowel movement or it is black and sticky like tar
- unusual weight gain
- skin rash or blisters with fever
- swelling of the arms, legs, hands and feet

If you take too much of your NSAID, call your healthcare provider or get medical help right away.

These are not all the possible side effects of NSAIDs. For more information, ask your healthcare provider or pharmacist about NSAIDs.

Call your doctor for medical advice about side effects. You may report side effects to FDA at 1-800-FDA-1088 or to INA Pharmaceutics, Inc. at 866.835.0469.

Other information about NSAIDs

- Aspirin is an NSAID but it does not increase the chance of a heart attack. Aspirin can cause bleeding in the brain, stomach, and intestines. Aspirin can also cause ulcers in the stomach and intestines.
- Some NSAIDs are sold in lower doses without a prescription (over-the counter). Talk to your healthcare provider before using over-the-counter NSAIDs for more than 10 days.

General information about the safe and effective use of NSAIDs

Medicines are sometimes prescribed for purposes other than those listed in a Medication Guide. Do not use NSAIDs for a condition for which it was not prescribed. Do not give NSAIDs to other people, even if they have the same symptoms that you have. It may harm them.

If you would like more information about NSAIDs, talk with your healthcare provider. You can ask your pharmacist or healthcare provider for information about NSAIDs that is written for health professionals.

Manufactured for:

INA Pharmaceutics Inc.

Fairmont, WV 26554

This Medication Guide has been approved by the U.S. Food and Drug Administration.

Revised: 06/2024

51U180000006US01

PACKAGE LABEL.PRINCIPAL DISPLAY PANEL - 250 mg

NDC 74157-009-60

DOLOBIDTM(Diflunisal) 250 mg

PHARMACIST:Dispense the Medication Guide provided separately to each patient.

60 Tablets

Rx only

PACKAGE LABEL.PRINCIPAL DISPLAY PANEL - 375 mg

NDC 74157-101-60

DOLOBIDTM (Diflunisal) 375 mg

PHARMACIST:Dispense the Medication Guide provided separately to each patient.

60 Tablets

Rx only